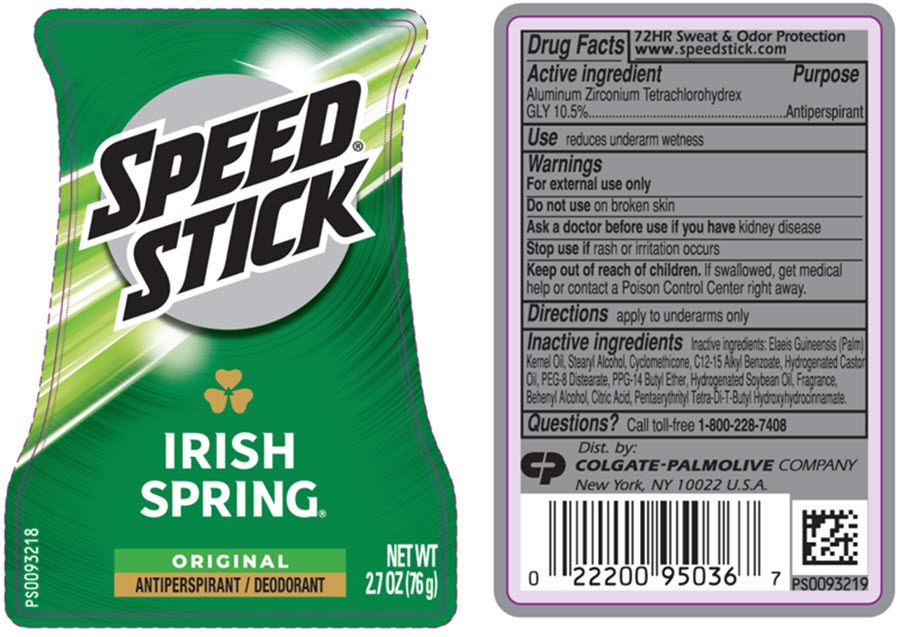 DRUG LABEL: Speed Stick
NDC: 35000-778 | Form: STICK
Manufacturer: Colgate-Palmolive Company
Category: otc | Type: HUMAN OTC DRUG LABEL
Date: 20260218

ACTIVE INGREDIENTS: ALUMINUM ZIRCONIUM TETRACHLOROHYDREX GLY 105 mg/1 g
INACTIVE INGREDIENTS: PALM KERNEL OIL; STEARYL ALCOHOL; CYCLOMETHICONE 5; ALKYL (C12-15) BENZOATE; HYDROGENATED CASTOR OIL; PEG-8 DISTEARATE; PPG-14 BUTYL ETHER; HYDROGENATED SOYBEAN OIL; DOCOSANOL; ANHYDROUS CITRIC ACID; PENTAERYTHRITOL TETRAKIS(3-(3,5-DI-TERT-BUTYL-4-HYDROXYPHENYL)PROPIONATE)

Speed® Stick
Irish Spring® Original

Drug Facts

Active ingredient

Aluminum Zirconium Tetrachlorohydrex GLY 10.5%

Purpose

Antiperspirant

Use

reduces underarm wetness

Warnings

For external use only

Do not use on broken skin

Ask a doctor before use if you have kidney disease

Stop use if rash or irritation occurs

Keep out of reach of children. If swallowed, get medical help or contact a Poison Control Center right away.

Directions

apply to underarms only

Inactive ingredients

Inactive ingredients: Elaeis Guineensis (Palm) Kernel Oil, Stearyl Alcohol, Cyclomethicone, C12-15 Alkyl Benzoate, Hydrogenated Castor Oil, PEG-8 Distearate, PPG-14 Butyl Ether, Hydrogenated Soybean Oil, Fragrance, Behenyl Alcohol, Citric Acid, Pentaerythrityl Tetra-Di-T-Butyl Hydroxyhydrocinnamate.

Questions?

Call toll-free 1-800-228-7408

Dist. by:
COLGATE-PALMOLIVE COMPANY
New York, NY 10022 U.S.A.

PRINCIPAL DISPLAY PANEL - 76 g Container Label

SPEED®
STICK

IRISH
SPRING®

ORIGINAL
ANTIPERSPIRANT / DEODORANT

NET WT
2.7 OZ (76 g)

PS0093218